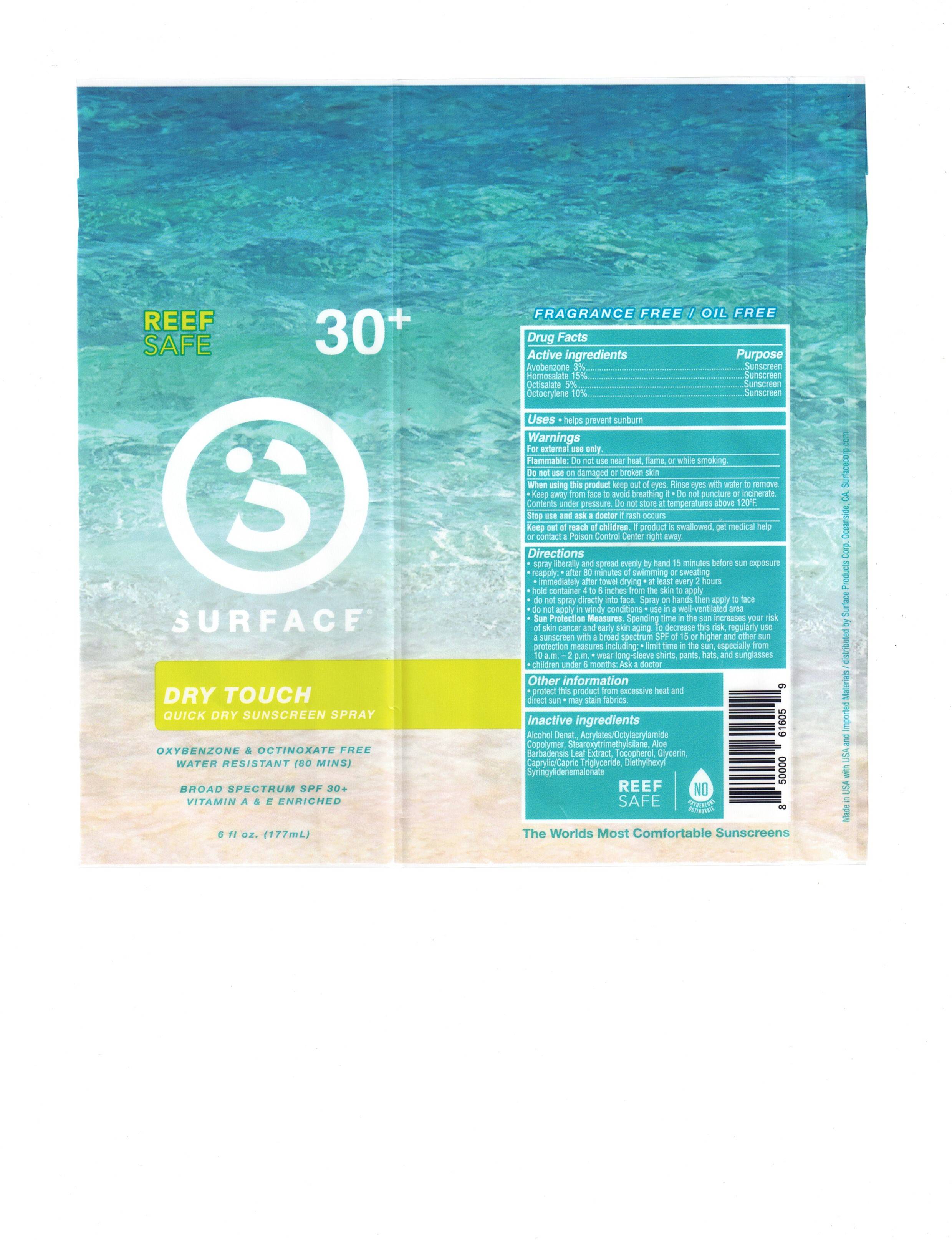 DRUG LABEL: Surface Sun Dry Touch SPF 50 Sunscreen
NDC: 72344-107 | Form: SPRAY
Manufacturer: Surface Products Corp
Category: otc | Type: HUMAN OTC DRUG LABEL
Date: 20260203

ACTIVE INGREDIENTS: AVOBENZONE 3 g/100 g; OCTISALATE 5 g/100 g; HOMOSALATE 15 g/100 g; OCTOCRYLENE 10 g/100 g
INACTIVE INGREDIENTS: CAPRYLIC/CAPRIC/LAURIC TRIGLYCERIDE; ALOE VERA LEAF; BEHENYL BEHENATE; DIETHYLHEXYL SYRINGYLIDENEMALONATE; GLYCERIN; TOCOPHEROL; ACRYLATE/ISOBUTYL METHACRYLATE/N-TERT-OCTYLACRYLAMIDE COPOLYMER (75000 MW); STEAROXYTRIMETHYLSILANE

Surface Sun Dry Touch SPF 50 Sunscreen Spray

Active ingredient

Avobenzone 3.0%

Homosalate 15%

Octisalate 5%

Octocrylene 10%

When using this product:

• keep out of eyes. Rinse with water to remove.

• Keep away from face to avoid breathing it.

• Do not puncture or incinerate, Contents under pressure

• Do not store at temperature above 120⁰F

Stop use and ask a doctor if rash occurs.

PURPOSE

Avobenzone 3.0% ……………………………………………………………………………… Sunscreen

Homosalate 15.0% ……………………………………………………………………………. Sunscreen

Octisalate 5.0% …………………………………………………………………………………. Sunscreen

Octocrylene 10.0% ……………………………………………………………………………. Sunscreen

Stop use and ask a doctor if rash occurs.

Keep out of reach of children. If swallowed, get medical help or contact a Poison Control Center right away.

INACTIVE INGREDIENT

Behenyl Alcohol

BHT

Butyloctyl Salicylate

Caprylyl Methicone Dimethicone

Dimethyl Capramide

Disodium EDTA

Ethylhexyl Stearate

Ethylhexylglycerin

Fragrance

Glyceryl Stearate Hydrated Silica

PEG-100 Stearate

Phenoxyethanol

Polyester-8

Sodium Polyacrylate

Styrene/Acrylates Copolymer

Trideceth-6

Trimethylsiloxysilicate

VP/Hexadecene Copolymer

Water

Xanthan Gum

WHEN USING

• keep out of eyes. Rinse with water to remove.

• Keep away from face to avoid breathing it.

• Do not puncture or incinerate, Contents under pressure

• Do not store at temperature above 120⁰F

Stop use and ask a doctor if rash occurs.

Uses

Warnings

uses